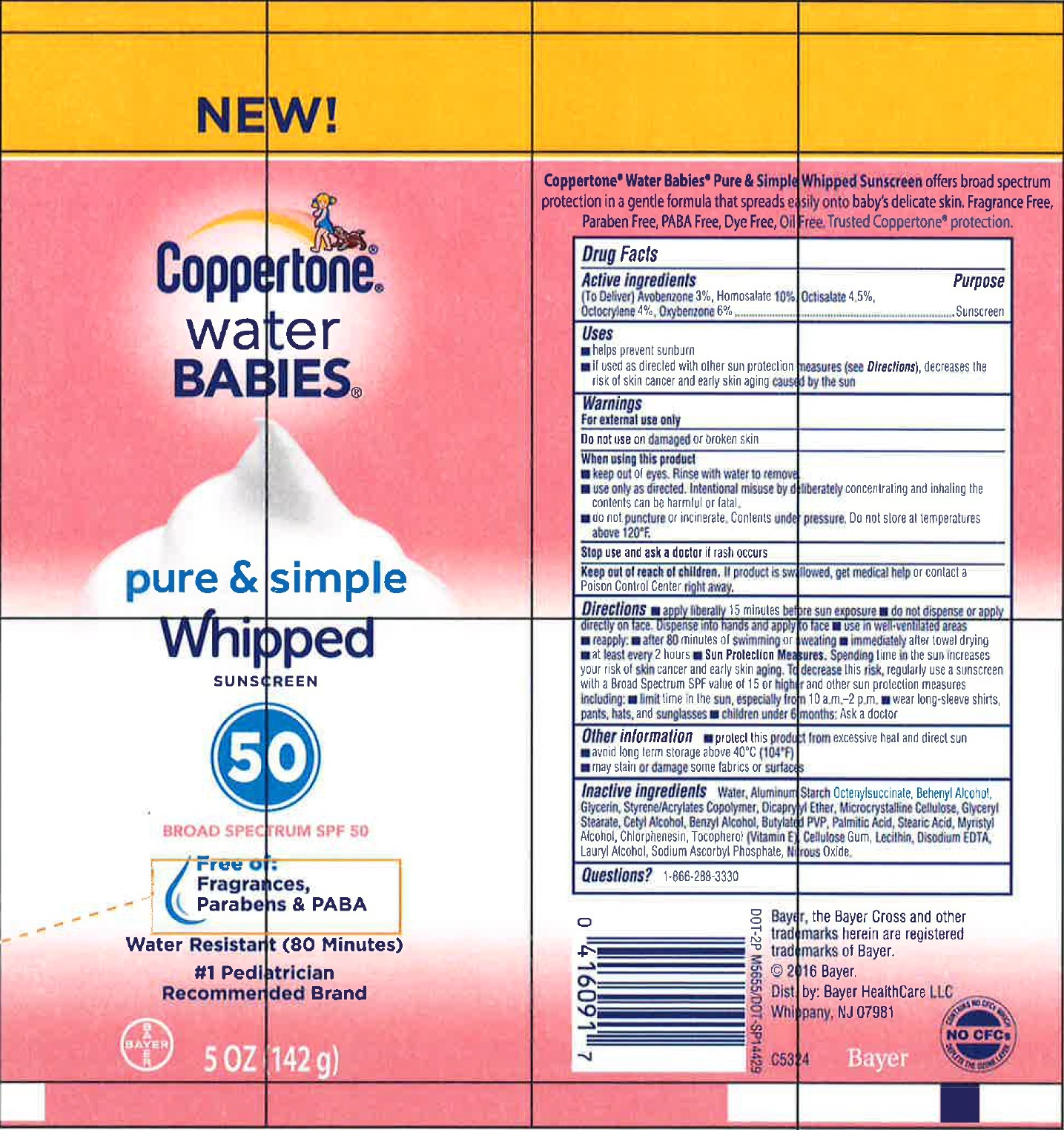 DRUG LABEL: Copperstone Water Babies Pure and Simple Whipped Sunscreen Broad Spectrum SPF 50
NDC: 23667-802 | Form: LOTION
Manufacturer: Formulated Solutions, LLC
Category: otc | Type: HUMAN OTC DRUG LABEL
Date: 20231202

ACTIVE INGREDIENTS: AVOBENZONE 30 mg/1 g; HOMOSALATE 100 mg/1 g; OCTISALATE 45 mg/1 g; OCTOCRYLENE 40 mg/1 g; OXYBENZONE 60 mg/1 g
INACTIVE INGREDIENTS: ALUMINUM STARCH OCTENYLSUCCINATE; WATER; DOCOSANOL; GLYCERIN; DICAPRYLYL ETHER; MICROCRYSTALLINE CELLULOSE; GLYCERYL MONOSTEARATE; CETYL ALCOHOL; BENZYL ALCOHOL; PALMITIC ACID; STEARIC ACID; MYRISTYL ALCOHOL; CHLORPHENESIN; TOCOPHEROL; CARBOXYMETHYLCELLULOSE SODIUM, UNSPECIFIED FORM; EDETATE DISODIUM ANHYDROUS; LAURYL ALCOHOL; SODIUM ASCORBYL PHOSPHATE; NITROUS OXIDE

Copperstone Water Babies Pure and Simple Whipped Sunscreen Broad Spectrum SPF 50

Active ingredients

(To Deliver) Avobenzone 3%, Homosalate 10%, Octisalate 4.5%,
Octocrylene 4%, Oxybenzone 6%

Purpose

Sunscreen

Uses

- helps prevent sunburn
- if used as directed with other sun protection increases (see Directions), decreases the risk of skin cancer and early skin aging caused by the sun

Warnings

For external use only

Do not use on

damaged or broken skin

When using this product

- keep out of eyes. Rinse with water to remove.
- use only as directed. Intentional misue by deliberately concentrating and inhaling the contents can be harmful or fatal.
- do not puncture or incinerate. Contents under pressure. Do not store at temperatures above 120°F.

Stop use and ask a doctor if

rash occurs

Keep out of reach of children.

If product is swallowed, get medical help or contact a Poison Control Center right away.

Directions

- apply liberally 15 minutes before sun exposure
- do not dispense or apply directly on face. Dispense into hands and apply to face
- use in well-ventillated areas
- reapply:
- after 80 minutes if swimming or sweating
- imediately after towel drying
- at least every 2 hours
- Sun Protection Measures. Spending time in the sun increases your risk of skin cancer and early skin aging. To decrease this risk, regularly use a sunscereen with a Broad Spectrum SPF value of 15 or higher and other sun protection measures including:
- limit time in the sun, especially from 10 a.m.-2 p.m.
- wear long-sleeve shirts, pants, hats, and sunglasses
- children under 6 months: Ask a doctor

Other Information

- protect this product from excessive heat and direct sun
- avoid long term storage above 40°C (104°F)
- may stain or damage some fabrics or surfaces

Inactive ingredients

Water, Aluminum Starch Octenylsuccinate, Behenyl Alcohol, Glycerin, Styrene/Acrylates Copolymer, Dicaprylyl Ether, Microcrystalline Cellulose, Glyceryl Stearate, Cetyl Alcohol, Benzyl Alcohol, Butylated PVP, Palmitic Acid, Stearic Acid, Myristyl Alcohol, Chlorphenesin, Tocopherol (Vitamin E), Cellulose Gum, Lecithin, Disodium EDTA, Lauryl Alcohol, Sodium Ascorbyl Phosphate, Fragrance, Nitrous Oxide.

Questions?

1-866-288-330